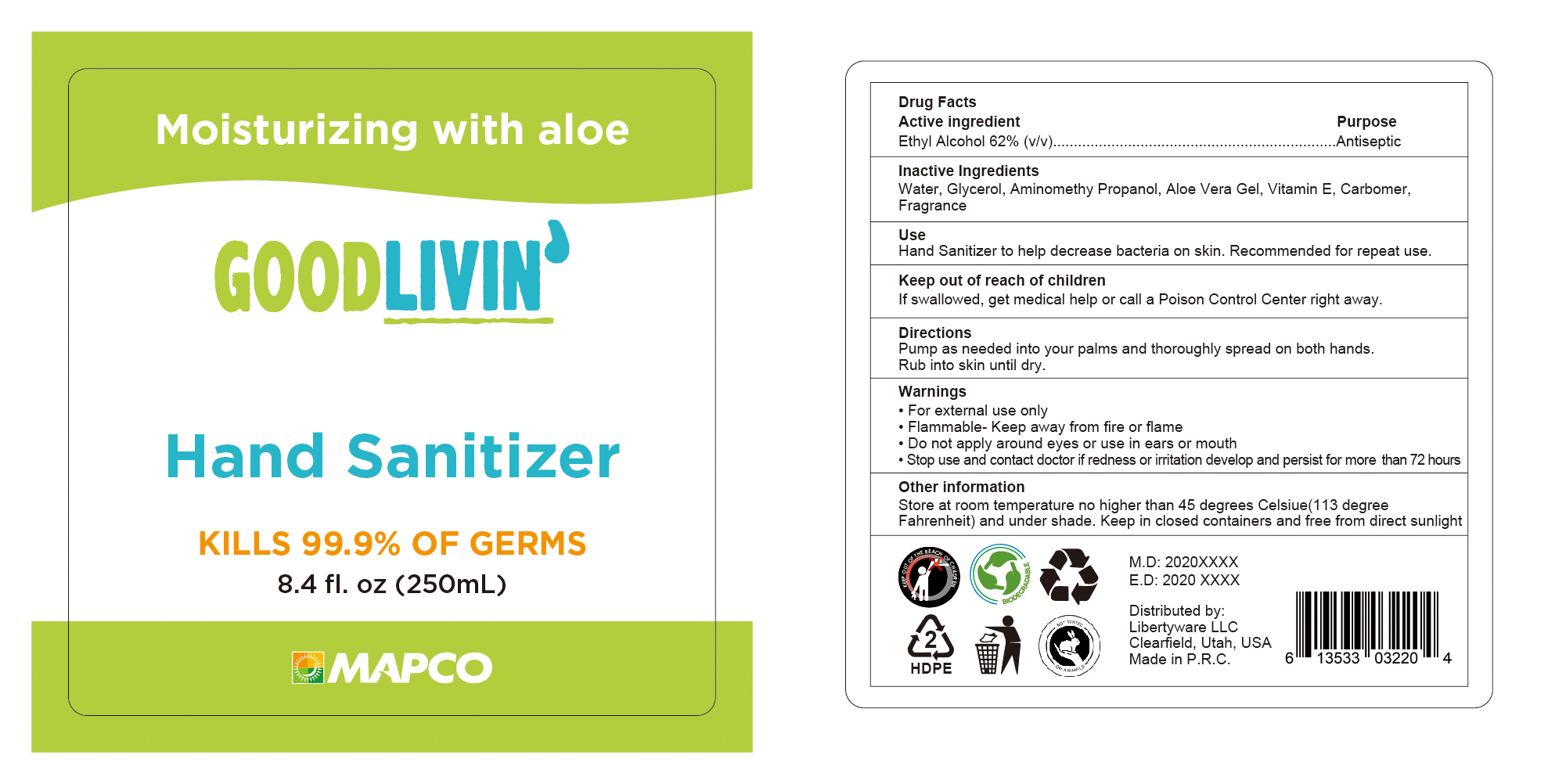 DRUG LABEL: GOODLIVIN Hand Sanitizer Moisturizing with Aloe
NDC: 52989-002 | Form: SOLUTION
Manufacturer: Taizhou Yadai Daily-Use Co., Ltd.
Category: otc | Type: HUMAN OTC DRUG LABEL
Date: 20200619

ACTIVE INGREDIENTS: ALCOHOL 62 mL/100 mL
INACTIVE INGREDIENTS: GLYCERIN; CARBOMER 934; TROLAMINE; AMINOMETHYLPROPANOL; ALOE VERA WHOLE; .ALPHA.-TOCOPHEROL ACETATE

52989-002

Active Ingredient(s)

Ethyl Alcohol 62% v/v

Purpose

Antiseptic

Use

Hand sanitizer to help decrease bacteria on the skin

Recommended for repeated use

Warnings

For external use only. Flammable. Keep away from fire or flame

Do not apply around eyes or use in ears or mouth

Stop use and contact a doctor if redness or irritation develop or persist for more than 72 hours

Keep out of reach of children. If swallowed, get medical help or call a Poison Control Center right away.

Directions

- Pump as needed into your palms and thoroughly spead on both hands
- rub into skin until dry

Other information

- Store at room temperature no higher than 45C (115F) and under shade
- Keep in closed containers and free direct sunlight

Inactive ingredients

Water, Glycerol, Aminomethyl propanol, Aloe Vera gel, Vitamin E, Carbomer, Frangrance